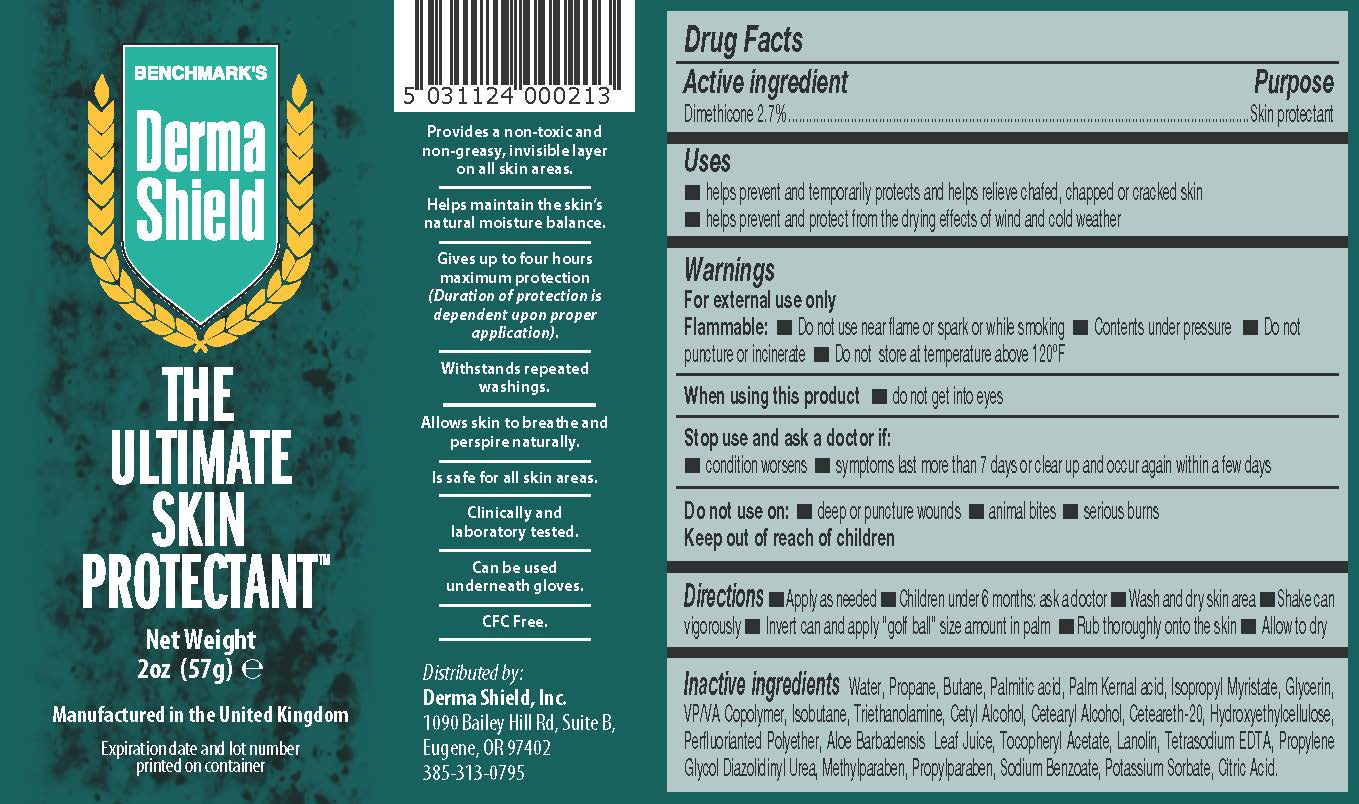 DRUG LABEL: Benchmarks Derma Shield
NDC: 70557-002 | Form: AEROSOL
Manufacturer: Delta Kits Inc
Category: otc | Type: HUMAN OTC DRUG LABEL
Date: 20231002

ACTIVE INGREDIENTS: DIMETHICONE 2.7 g/100 g
INACTIVE INGREDIENTS: LANOLIN; PROPYLPARABEN; POLYOXYL 20 CETOSTEARYL ETHER; CITRIC ACID MONOHYDRATE; DIAZOLIDINYL UREA; GLYCERIN; HYDROXYETHYL CELLULOSE (4000 MPA.S AT 1%); METHYLPARABEN; PALM KERNEL ACID; PROPYLENE GLYCOL; SODIUM BENZOATE; COPOVIDONE K25-31; EDETATE SODIUM; .ALPHA.-TOCOPHEROL ACETATE; TROLAMINE; ALOE VERA LEAF; WATER; CETYL ALCOHOL; ISOBUTANE; ISOPROPYL MYRISTATE; PALMITIC ACID; PERFLUOROPOLYMETHYLISOPROPYL ETHER; POTASSIUM SORBATE; PROPANE; BUTANE

Benchmarks Derma Shield

Active ingredient

Dimethicone, 2.7%

Purpose

Skin protectant

Do not use on:

- deep or puncture wounds
- animal bites
- serious burns
- Keep out of reach of children

Uses

- helps prevent and temporarily protects and helps relieve chafed, chapped, or cracked skin
- helps prevent and protect from the drying effects or wind and cold weather

Warnings

For external use only

Flammable:

- Do not use near flame or spark or while smoking
- Contents under pressure
- Do not puncture or incinerate
- Do not store at temperature above 120oF

Directions

- Apply as needed
- Children under 6 months: ask a doctor
- Wash and dry skin area
- Shake can vigorously
- Invert can and apply "golf ball" size amount in palm
- Rub thoroughly onto the skin
- Alllow to dry

Inactive ingredients

Water, Propane, Butane, Palmitic acid, Palm Kernal acid, Isopropyl Myrisate, Glycerin,

VP/VA Copolymer, Isobutane, Triethanolamine, Cetyl Alcohol, Cetearyl Alcohol, Ceteareth-20, Hydroxyethylcellulose,

Perfluorianted Polyether, Aloe Barbadensis Leaf Juice, Tocopheryl Acetate, Lanolin, Tetrasodium EDTA, Propylene Glycol Diazolindinyl Urea, Methylparaben, Propylparaben, Sodium Benzoate, Potassium Sorbate, Citric Acid